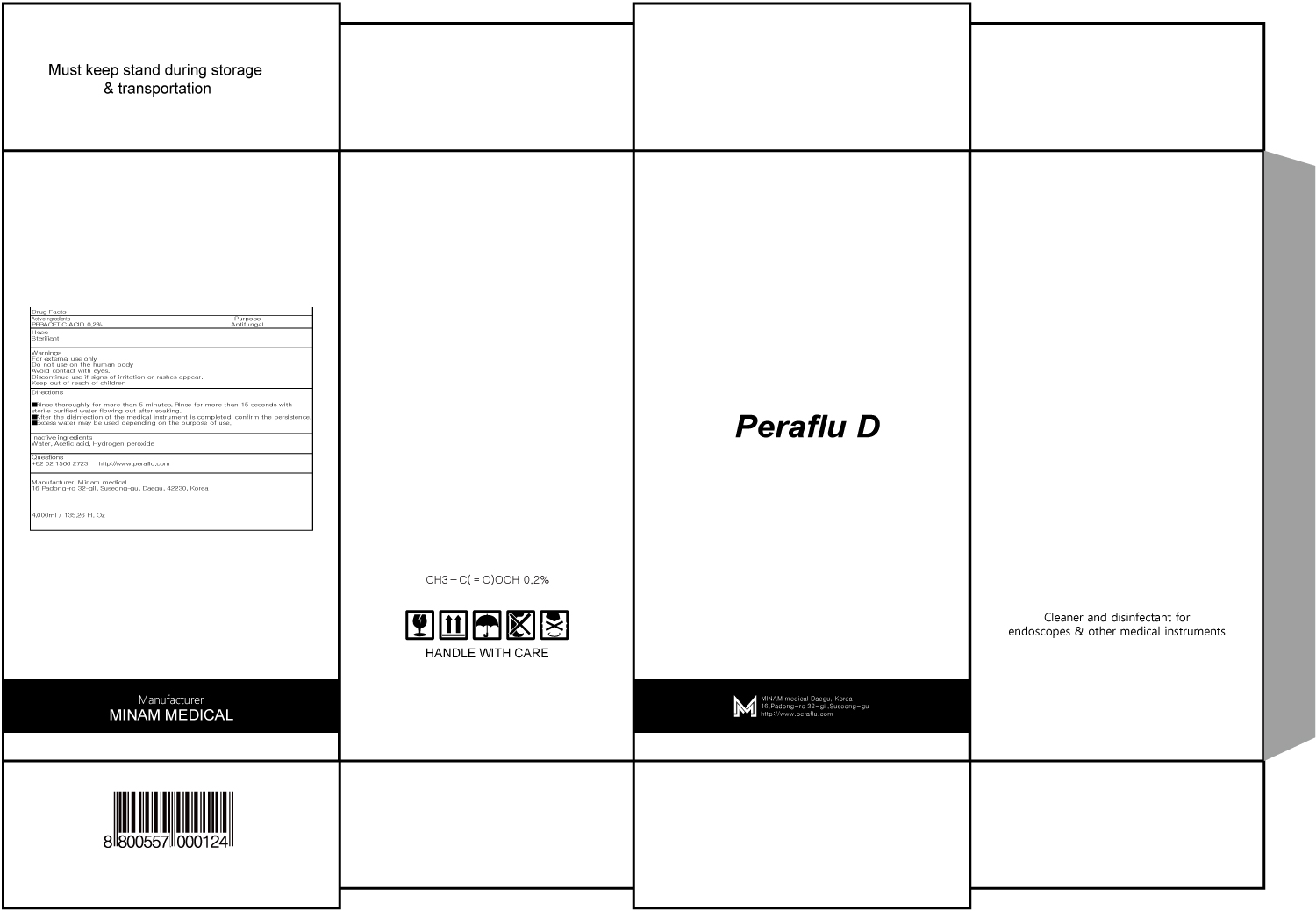 DRUG LABEL: Peraflu D
NDC: 72329-010 | Form: LIQUID
Manufacturer: minam medical
Category: otc | Type: HUMAN OTC DRUG LABEL
Date: 20180530

ACTIVE INGREDIENTS: PERACETIC ACID 8.0 g/4000 mL
INACTIVE INGREDIENTS: Water; Acetic acid

ACTIVE INGREDIENT

Active ingredients: PERACETIC ACID 0.2%

INACTIVE INGREDIENT

Inactive ingredients:

Water, Acetic acid, Hydrogen peroxide

PURPOSE

Purpose: Antifungal

WARNINGS

For external useonly

Do not use on the human body

Avoid contact with eyes.

Discontinue use if signs of irritation or rashes appear.

Keep out of reach of children

KEEP OUT OF REACH OF CHILDREN

Uses

Steriliant

Directions

- Rinse thoroughly for more than 5 minutes. Rinse for more than 15 seconds with sterile purified water flowing out after soaking.

- After the disinfection of the medical instrument is completed, confirm the persistence.

- Excess water may be used depending on the purpose of use.